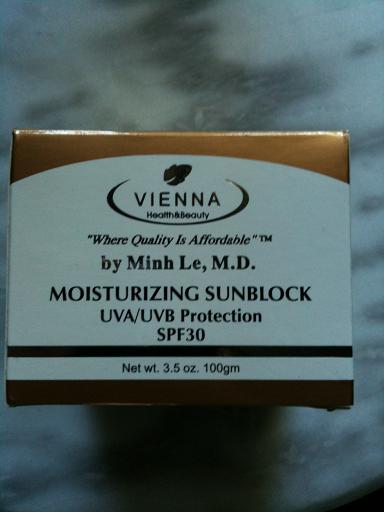 DRUG LABEL: Moisturizing Sunblock
NDC: 52625-100 | Form: LOTION
Manufacturer: Vienna Health and Beauty Corporation
Category: otc | Type: HUMAN OTC DRUG LABEL
Date: 20100701

ACTIVE INGREDIENTS: TITANIUM DIOXIDE 8 g/100 g; OCTINOXATE 6 g/100 g; BENZOPHENONE 3 g/100 g

Drug Facts

Active Ingredients: Purpose
Titanium Dioxide 8% Sunscreen
Octyl Methoxycinnamate 6% Sunscreen
Benzophenone 3% Sunscreen
Other Ingredients: Purified Water (Acqua), Capryic/Capic Triglyceride, C12-15 Alkyl Benzoate, Glycerin, Cetyl Alcohol, Stearyl Alcohol, Isopropyl Myristate, Propylene Glycol, Ceteareth-6,Ceteareth-25, Dimethocone, Glyceryl Stearate, Stearic Acid, Tocopherol Acetate9Vitamin E), Alpha Bisabolol, Triethanolamine, Diazolidinyl Urea, Methylparaben, Propylparaben, Allantoin, BHT.

PACKAGE LABEL

Vienna Health and Beauty - MOISTURIZING SUNBLOCK - UVA/UVB Protection - SPF30